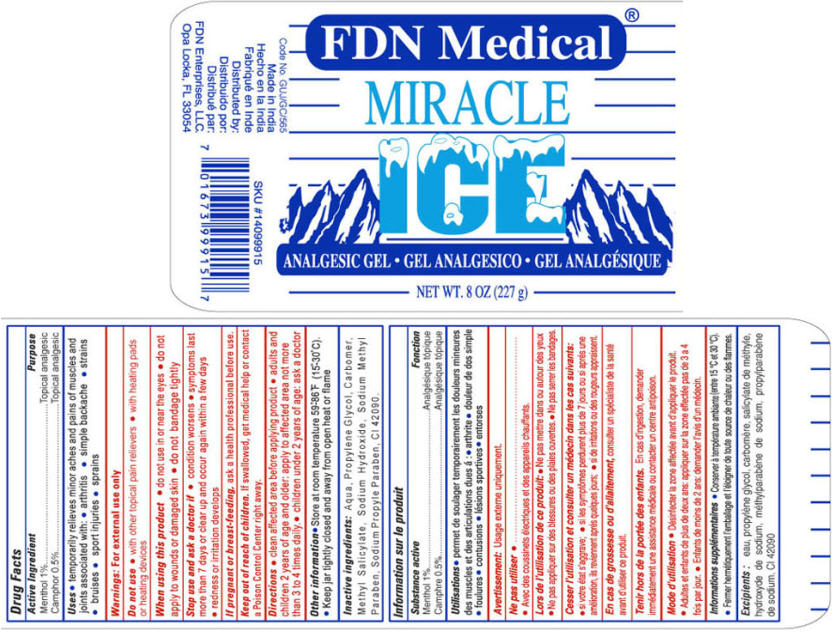 DRUG LABEL: MIRACLE ICE
NDC: 60691-115 | Form: GEL
Manufacturer: FDN Enterprises, LLC
Category: otc | Type: HUMAN OTC DRUG LABEL
Date: 20130923

ACTIVE INGREDIENTS: Menthol 1 g/100 g; Camphor (synthetic) 0.5 g/100 g
INACTIVE INGREDIENTS: Water; Propylene Glycol; Methyl Salicylate; Sodium Hydroxide; METHYLPARABEN SODIUM; PROPYLPARABEN SODIUM; FD&C BLUE NO. 1

MIRACLE ICE

Drug Facts

ACTIVE INGREDIENT

Active Ingredient | Purpose
Menthol 1% | Topical analgesic
Camphor 0.5% | Topical analgesic

Uses

- temporarily relieves minor aches and pains of muscles and joints associated with:
  - arthritis
  - simple backache
  - strains
  - bruises
  - sport injuries
  - sprains

Warnings

For external use only

Do not use

- with other topical pain relievers
- with heating pads or heating devices

When using this product

- do not use in or near the eyes
- do not apply to wounds or damaged skin
- do not bandage tightly

Stop use and ask a doctor if

- condition worsens
- symptoms last more than 7 days or clear up and occur again within a few days
- redness or irritation develops

PREGNANCY OR BREAST FEEDING

If pregnant or breast-feeding, ask a health professional before use.

Keep out of reach of children. If swallowed, get medical help or contact a Poison Control Center right away.

Directions

- clean affected area before applying product
- adults and children 2 years of age and older: apply to affected area not more than 3 to 4 times daily.
- children under 2 years of age: ask a doctor

Other information

- Store at room temperature 59°-86°F (15°-30°C).
- Keep jar tightly closed and away from open heat or flame

Inactive ingredients

Aqua, Propylene Glycol, Carbomer, Methyl Salicylate, Sodium Hydroxide, Sodium Methyl Paraben, Sodium Propyle Paraben, CI 42090.

Distributed by:
FDN Enterprises, LLC.
Opa Locka, FL 33054

PRINCIPAL DISPLAY PANEL - 277 g Jar Label

FDN Medical®

MIRACLE
ICE

ANALGESIC GEL

NET WT. 8 OZ (277 g)